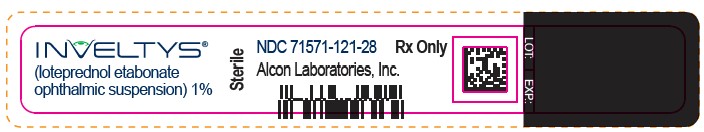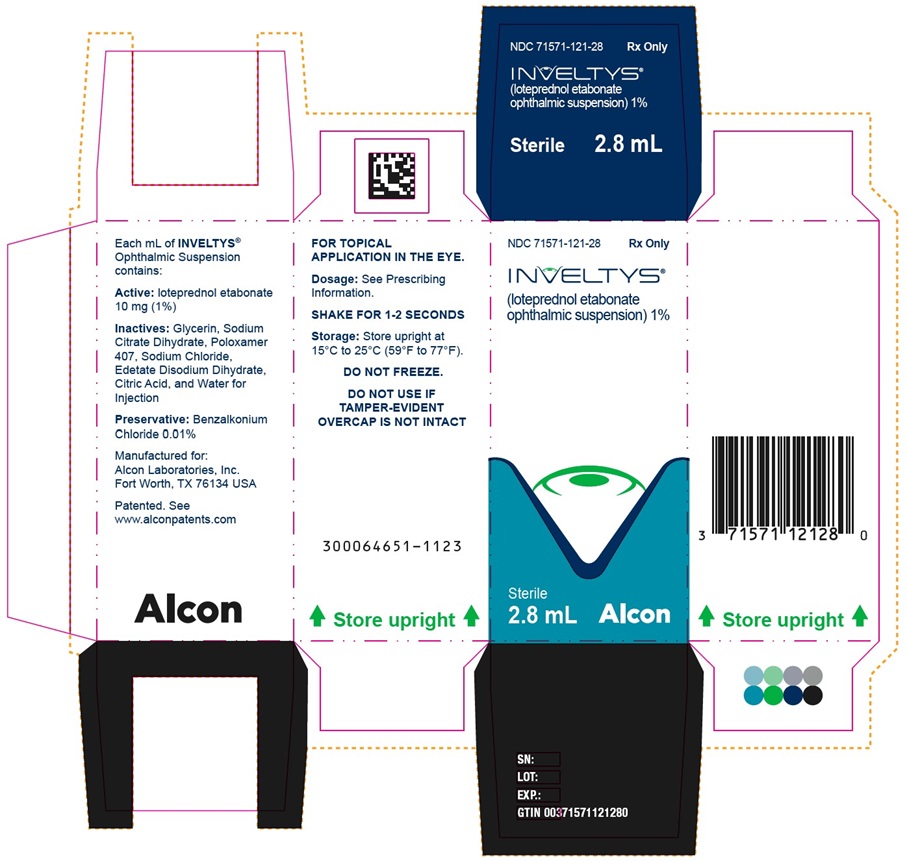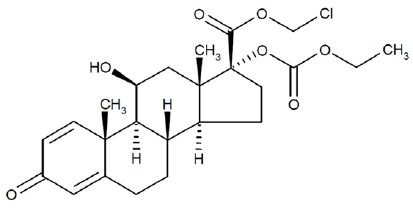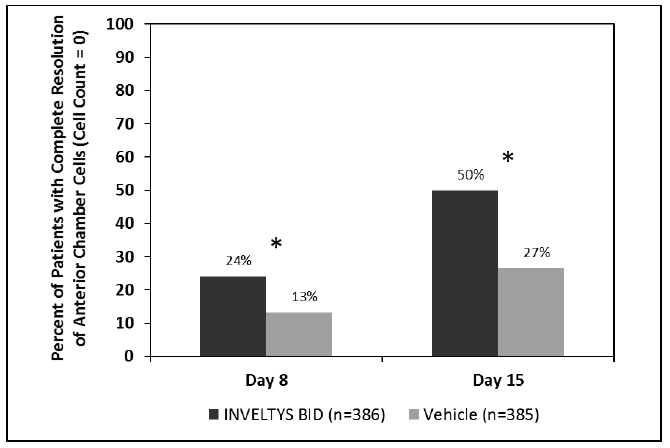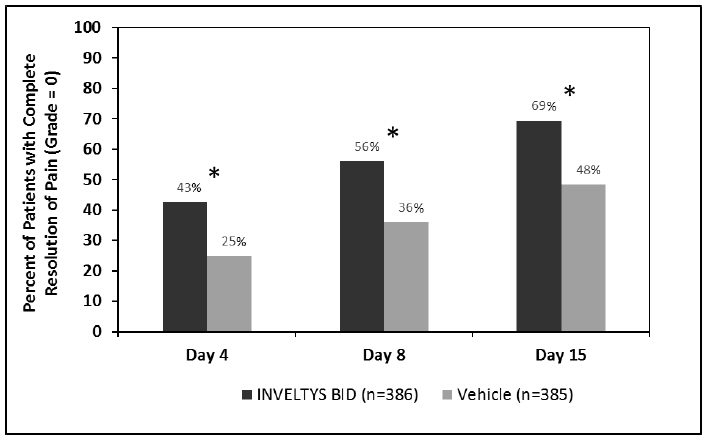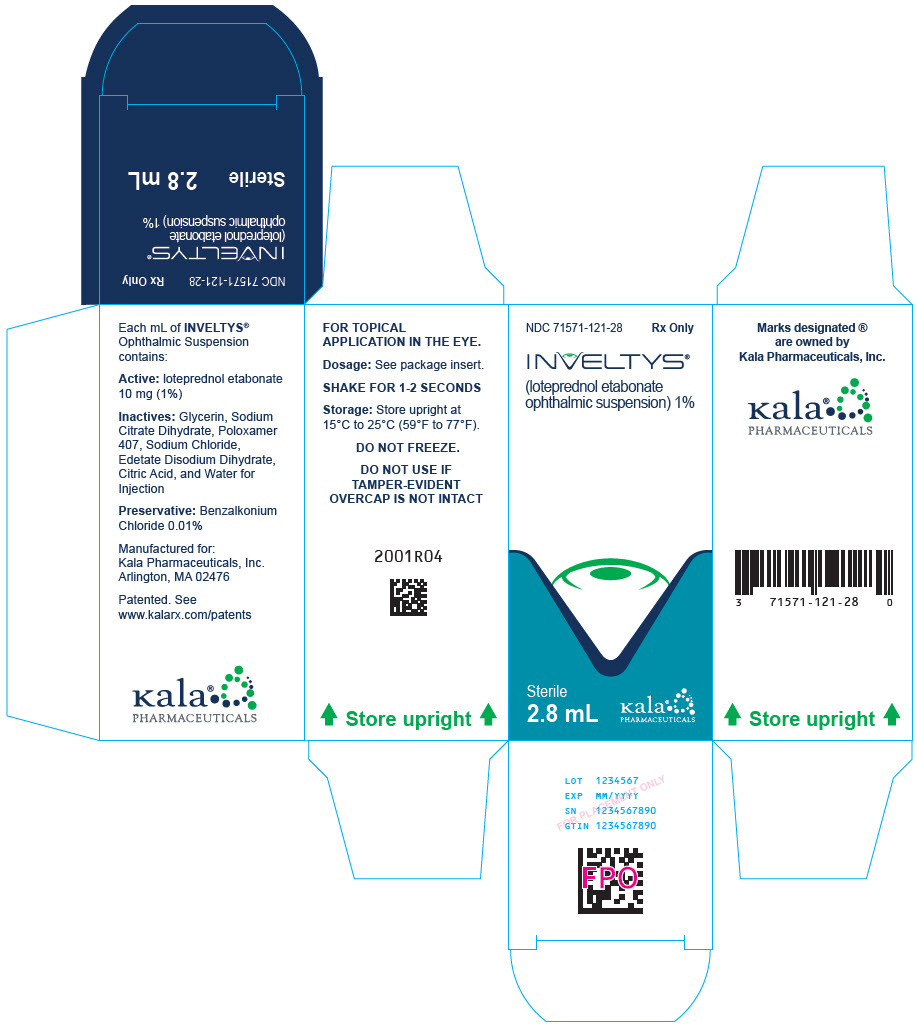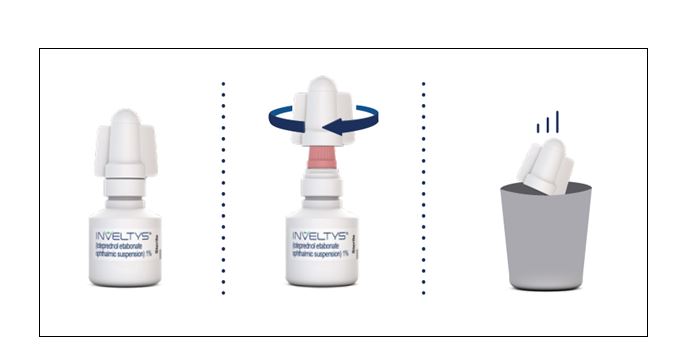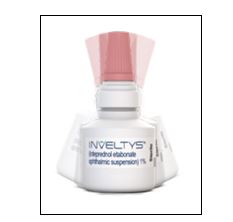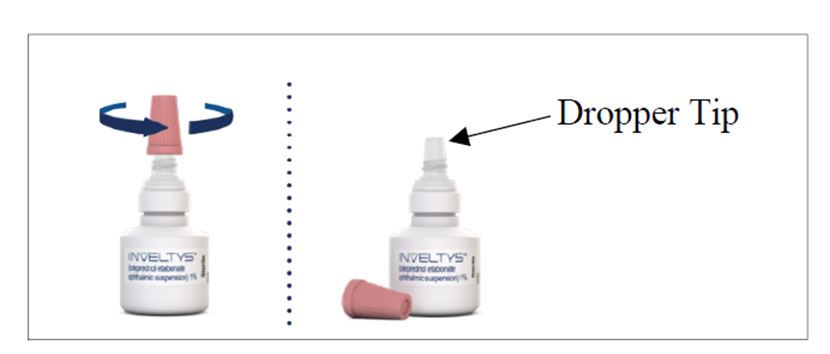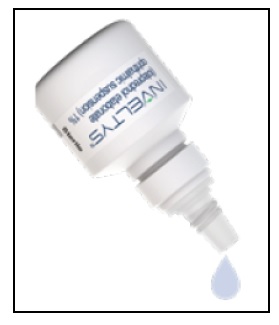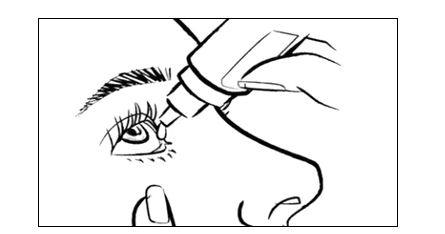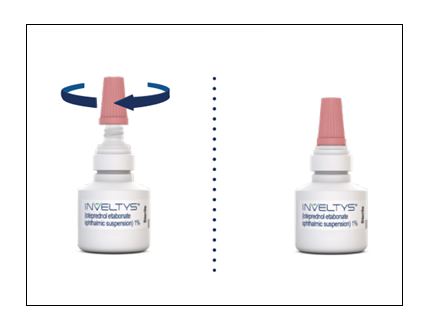 DRUG LABEL: Inveltys
NDC: 71571-121 | Form: SUSPENSION
Manufacturer: ALCON LABORATORIES, INC.
Category: prescription | Type: HUMAN PRESCRIPTION DRUG LABEL
Date: 20240327

ACTIVE INGREDIENTS: LOTEPREDNOL ETABONATE 10 mg/1 mL
INACTIVE INGREDIENTS: GLYCERIN; TRISODIUM CITRATE DIHYDRATE; SODIUM CHLORIDE; EDETATE DISODIUM; CITRIC ACID MONOHYDRATE; WATER

HIGHLIGHTS OF PRESCRIBING INFORMATION

These highlights do not include all the information needed to use INVELTYS® safely and effectively. See full prescribing information for INVELTYS.
INVELTYS (loteprednol etabonate ophthalmic suspension) 1%, for topical ophthalmic use
Initial U.S. Approval: 1998

1 INDICATIONS AND USAGE

INVELTYS is a corticosteroid indicated for the treatment of post-operative inflammation and pain following ocular surgery. (1)

2 DOSAGE AND ADMINISTRATION

- Shake for one to two seconds before using. (2)
- Instill one to two drops of INVELTYS into the affected eye twice daily beginning the day after surgery and continuing throughout the first 2 weeks of the post-operative period. (2)

3 DOSAGE FORMS AND STRENGTHS

Ophthalmic suspension containing 10 mg/mL of loteprednol etabonate. (3)

4 CONTRAINDICATIONS

INVELTYS is contraindicated in most viral diseases of the cornea and conjunctiva including epithelial herpes simplex keratitis (dendritic keratitis), vaccinia, and varicella, and also in mycobacterial infection of the eye and fungal diseases of ocular structures. (4)

5 WARNINGS AND PRECAUTIONS

- Intraocular Pressure (IOP) Increase: Prolonged use of corticosteroids may result in glaucoma with damage to the optic nerve, defects in visual acuity and fields of vision. If this product is used for 10 days or longer, IOP should be monitored. (5.1)
- Cataracts: Use of corticosteroids may result in posterior subcapsular cataract formation. (5.2)
- Delayed Healing: Use of steroids after cataract surgery may delay healing and increase the incidence of bleb formation. In those diseases causing thinning of the cornea or sclera, perforations have been known to occur with the use of topical steroids. The initial prescription and renewal of the medication order should be made by a physician only after examination of the patient with the aid of magnification such as slit lamp biomicroscopy and, where appropriate, fluorescein staining. (5.3)
- Bacterial Infections: Prolonged use of corticosteroids may suppress the host response and thus increase the hazard of secondary ocular infections. In acute purulent conditions, steroids may mask infection or enhance existing infection. (5.4)
- Viral Infections: Use of a corticosteroid medication in the treatment of patients with a history of herpes simplex requires great caution. Use of ocular steroids may prolong the course and may exacerbate the severity of many viral infections of the eye (including herpes simplex). (5.5)
- Fungal Infections: Fungal infections of the cornea are particularly prone to develop coincidentally with long-term local steroid application. Fungus invasion must be considered in any persistent corneal ulceration where a steroid has been used or is in use. (5.6)

6 ADVERSE REACTIONS

The most common adverse drug reactions were eye pain (1%) and posterior capsular opacification (1%). These reactions may have been the consequence of the surgical procedure. (6)

To report SUSPECTED ADVERSE REACTIONS, contact Alcon Laboratories, Inc. at 1-800-757-9195 or FDA at 1-800-FDA-1088 or www.fda.gov/medwatch.

FULL PRESCRIBING INFORMATION

1 INDICATIONS AND USAGE

INVELTYS is a corticosteroid indicated for the treatment of post-operative inflammation and pain following ocular surgery.

2 DOSAGE AND ADMINISTRATION

2.1 Dosage Information

Instill one to two drops of INVELTYS into the affected eye twice daily beginning the day after surgery and continuing throughout the first 2 weeks of the post-operative period.

2.2 Administration Instructions

Instruct patient to wash hands well before each use.

Shake for one to two seconds before using.

If the patient is using other eye drops in addition to INVELTYS, advise the patient to wait at least 5 minutes between instillation of INVELTYS and other eye drops.

3 DOSAGE FORMS AND STRENGTHS

Ophthalmic suspension containing 10 mg/mL of loteprednol etabonate.

4 CONTRAINDICATIONS

INVELTYS is contraindicated in most viral diseases of the cornea and conjunctiva including epithelial herpes simplex keratitis (dendritic keratitis), vaccinia, and varicella, and also in mycobacterial infection of the eye and fungal diseases of ocular structures.

5 WARNINGS AND PRECAUTIONS

5.1 Intraocular Pressure (IOP) Increase

Prolonged use of corticosteroids may result in glaucoma with damage to the optic nerve, as well as defects in visual acuity and fields of vision. Steroids should be used with caution in the presence of glaucoma. If this product is used for 10 days or longer, intraocular pressure should be monitored.

5.2 Cataracts

Use of corticosteroids may result in posterior subcapsular cataract formation.

5.3 Delayed Healing

Use of steroids after cataract surgery may delay healing and increase the incidence of bleb formation. In those diseases causing thinning of the cornea or sclera, perforations have been known to occur with the use of topical steroids. The initial prescription and renewal of the medication order should be made by a physician only after examination of the patient with the aid of magnification such as slit lamp biomicroscopy and, where appropriate, fluorescein staining.

5.4 Bacterial Infections

Prolonged use of corticosteroids may suppress the host response and thus increase the hazard of secondary ocular infections. In acute purulent conditions of the eye, steroids may mask infection or enhance existing infection.

5.5 Viral Infections

Use of corticosteroid medication in the treatment of patients with a history of herpes simplex requires great caution. Use of ocular steroids may prolong the course and may exacerbate the severity of many viral infections of the eye (including herpes simplex).

5.6 Fungal Infections

Fungal infections of the cornea are particularly prone to develop coincidentally with long-term local steroid application. Fungus invasion must be considered in any persistent corneal ulceration where a steroid has been used or is in use. Fungal cultures should be taken when appropriate.

5.7 Risk of Contamination

Do not to allow the dropper tip to touch any surface, as this may contaminate the suspension.

5.8 Contact Lens Wear

The preservative in INVELTYS may be absorbed by soft contact lenses. Contact lenses should be removed prior to instillation of INVELTYS and may be reinserted 15 minutes following administration.

6 ADVERSE REACTIONS

Adverse reactions associated with ophthalmic steroids include elevated intraocular pressure, which may be associated with infrequent optic nerve damage, visual acuity and field defects, posterior subcapsular cataract formation, delayed wound healing and secondary ocular infection from pathogens including herpes simplex, and perforation of the globe where there is thinning of the cornea or sclera.

6.1 Clinical Trials Experience

Because clinical trials are conducted under widely varying conditions, adverse reaction rates observed in the clinical trials of a drug cannot be directly compared to rates in the clinical trials of another drug and may not reflect the rates observed in practice.

The most common adverse drug reactions in the clinical trials with INVELTYS were eye pain and posterior capsular opacification, both reported in 1% of patients. These reactions may have been the consequence of the surgical procedure.

8 USE IN SPECIFIC POPULATIONS

8.1 Pregnancy

Risk Summary

INVELTYS is not absorbed systemically following topical ophthalmic administration and maternal use is not expected to result in fetal exposure to the drug.

8.2 Lactation

Risk Summary

INVELTYS is not absorbed systemically by the mother following topical ophthalmic administration, and breastfeeding is not expected to result in exposure of the child to INVELTYS.

8.3 Pediatric Use

Safety and effectiveness in pediatric patients have not been established.

8.4 Geriatric Use

No overall differences in safety and effectiveness have been observed between elderly and younger patients.

11 DESCRIPTION

Loteprednol etabonate is a corticosteroid. Its chemical name is chloromethyl 17α-[(ethoxycarbonyl)oxy]-11β-hydroxy-3-oxoandrosta-1,4-diene-17β-carboxylate. Its molecular formula is C24H31ClO7 and its chemical structure is:

C24H31ClO7
Mol. Wt. 467.0

INVELTYS (loteprednol etabonate ophthalmic suspension) 1% contains a sterile, topical anti-inflammatory corticosteroid for ophthalmic use. Each mL contains:

- ACTIVE: loteprednol etabonate 10 mg (1%)
- INACTIVES: glycerin, sodium citrate dihydrate, Poloxamer 407, sodium chloride, edetate disodium dihydrate, citric acid, and water for injection
- PRESERVATIVE: benzalkonium chloride 0.01%

12 CLINICAL PHARMACOLOGY

12.1 Mechanism of Action

Corticosteroids inhibit the inflammatory response to a variety of inciting agents and probably delay or slow healing. They inhibit the edema, fibrin deposition, capillary dilation, leukocyte migration, capillary proliferation, fibroblast proliferation, deposition of collagen, and scar formation associated with inflammation. While glucocorticoids are known to bind to and activate the glucocorticoid receptor, the molecular mechanisms involved in glucocorticoid/glucocorticoid receptor-dependent modulation of inflammation are not clearly established. However, corticosteroids are thought to inhibit prostaglandin production through several independent mechanisms.

12.3 Pharmacokinetics

Loteprednol etabonate is lipid soluble and can penetrate into cells. Loteprednol etabonate is synthesized through structural modifications of prednisolone-related compounds so that it will undergo a predictable transformation to an inactive metabolite. Based upon in vivo and in vitro preclinical metabolism studies, loteprednol etabonate undergoes extensive metabolism to inactive carboxylic acid metabolites, PJ-91 and PJ-90.

Following twice-daily unilateral topical ocular dosing of INVELTYS for 14 days in healthy subjects, the plasma concentrations of loteprednol etabonate were below the limit of quantitation (1 ng/mL) at all timepoints.

13 NONCLINICAL TOXICOLOGY

13.1 Carcinogenesis, Mutagenesis, Impairment of Fertility

Long-term animal studies have not been conducted to evaluate the carcinogenic potential of loteprednol etabonate. Loteprednol etabonate was not genotoxic in vitro in the Ames test, the mouse lymphoma thymidine kinase (tk) assay, or in a chromosome aberration test in human lymphocytes, or in vivo in the single dose mouse micronucleus assay.

14 CLINICAL STUDIES

Clinical efficacy was evaluated in 2 multi-centered, randomized, double-masked, placebo-controlled trials in which patients with an anterior cell grade greater than or equal to "2" (a cell count of 6 or higher using a slit-lamp biomicroscope) after cataract surgery were assigned to INVELTYS or placebo (vehicle) following surgery (NCT # 02163824 and NCT # 02793817). One to two drops of INVELTYS or vehicle was self-administered twice a day for 14 days, beginning the day after surgery. Complete resolution of inflammation (a cell count of 0 maintained through day 15 without rescue medication) and complete resolution of pain (a patient-reported pain grade of 0 maintained through day 15 without rescue medication) was assessed 4, 8, and 15 days post-surgery. In the intent-to-treat analysis of both studies, a significant benefit was seen in the INVELTYS-treated group for complete resolution of ocular inflammation at Days 8 and 15, and complete resolution of pain at Days 4, 8, and 15, when compared with placebo. The consolidated clinical trial results are provided below.

Figure 1 Consolidated Clinical Trial Data: Percent of Patients with Complete Resolution of Anterior Chamber Cells (Cell Count = 0) at Days 8 and 15

* p-values < 0.01 for treatment comparisons

Figure 2 Consolidated Clinical Trial Data: Percent of Patients Who Were Pain Free at Days 4, 8, and 15

* p-values < 0.01 for treatment comparisons

16 HOW SUPPLIED/STORAGE AND HANDLING

INVELTYS (loteprednol etabonate ophthalmic suspension) 1% is a sterile ophthalmic suspension. It is supplied in a white low-density polyethylene plastic dropper bottle with a controlled-drop linear low-density polyethylene tip, a pink high-density polyethylene cap, and a white low-density polyethylene tamper-evident overcap in the following size:

2.8 mL in a 5 mL bottle (NDC 71571-121-28)

Storage and Handling

Do not use if tamper-evident overcap seal is not intact.

The white tamper-evident overcap can be thrown away. Retain the pink cap and keep the bottle tightly closed when not in use.

Store upright at 15°C to 25°C (59°F to 77°F). Do not freeze.

17 PATIENT COUNSELING INFORMATION

Administration

Instruct the patient to shake the bottle for one to two seconds before using. If the patient is using other eye drops in addition to INVELTYS, advise the patient to wait at least 5 minutes between instillation of INVELTYS and other eye drops.

Risk of Contamination

Advise patients to wash their hands well before each use. Advise patients not to allow the dropper tip to touch any surface, as this may contaminate the suspension.

Risk of Secondary Infection

Advise the patient to consult a physician if pain develops, or redness, itching, or inflammation becomes aggravated.

Contact Lens Wear

Advise patients that the preservative in INVELTYS may be absorbed by soft contact lenses. Contact lenses should be removed prior to instillation of INVELTYS and may be reinserted after 15 minutes following administration.

Manufactured for:

Alcon Laboratories, Inc.
Fort Worth, TX 76134 USA
U.S. Pat.: www.alconpatents.com

© 2023 Alcon Inc.
Alcon

INSTRUCTIONS FOR USE

INVELTYS [in-vel-tis]
(loteprednol etabonate ophthalmic suspension) 1%
for topical ophthalmic use

This Instructions for Use contains information on how to properly administer INVELTYS.

Important Information You Need to Know Before Using INVELTYS

- INVELTYS is for use in the eye only.
- Wash your hands before using INVELTYS.
- Do not use if the tamper-evident seal is not intact.
- Do not let the INVELTYS dropper tip touch your eye, fingers, or any other surfaces to avoid contamination or injury to your eye.
- Use INVELTYS exactly as your healthcare provider tells you to.
- If you are using INVELTYS with other eye (ophthalmic) medicines, you should wait at least 5 minutes between using INVELTYS and the other medicine.
- If you wear contact lenses, remove them before using INVELTYS.
- Put the pink cap back on INVELTYS after each use.

Before you use INVELTYS for the first time:

There are two caps on your bottle of INVELTYS. Hold the bottle firmly by its neck. Remove the white cap by twisting it clockwise (See Figure A). Throw away the white cap. INVELTYS is now ready to use.

Figure A

Follow Steps 1 to 6 each time you use INVELTYS.

Step 1. | Wash your hands well.
Step 2. | Shake the INVELTYS bottle for 1 to 2 seconds (See Figure B).
 | Figure B
Step 3: | Remove the pink cap from the top of the INVELTYS dropper by turning it counterclockwise (See Figure C). Keep the pink cap. Do not let the INVELTYS dropper tip touch your eye, fingers, or any other surface.
 | Figure C
Step 4: | Turn the INVELTYS bottle upside down (See Figure D).
 | Figure D
Step 5: | Tilt your head back. Hold the bottle directly above your affected eye. Squeeze the middle of the INVELTYS bottle gently to put 1 to 2 drops (follow your doctor's recommendation) into the affected eye (See Figure E).
 | Figure E
Step 6: | Place the pink cap back onto the INVELTYS bottle and tighten by turning clockwise (See Figure F).
 | Figure F

If you use contact lenses, wait for 15 minutes before placing them back in.

How should I store INVELTYS?

- Store INVELTYS upright at 59ºF to 77ºF (15ºC to 25ºC).
- Do not freeze.

Keep INVELTYS and all medicines out of the reach of children.

This Instructions for Use has been approved by the U.S. Food and Drug Administration.

Manufactured for:

Alcon Laboratories, Inc.
Fort Worth, TX 76134 USA

Revised: 11/2023

PRINCIPAL DISPLAY PANEL - 2.8 mL Bottle Carton

NDC 71571-121-28
Rx Only
INVELTYS®
(loteprednol etabonate ophthalmic suspension)1%
Sterile
2.8 mL
kala®
PHARMACEUTICALS

NDC 71571-121-28
Rx Only

INVELTYS®
(loteprednol etabonate
ophthalmic suspension) 1%

Sterile
2.8 mL

Alcon

FOR TOPICAL
APPLICATION IN THE EYE.
Dosage: See Prescribing
Information.
SHAKE FOR 1-2 SECONDS
Storage: Store upright at
15°C to 25°C (59°F to 77°F).
DO NOT FREEZE.
DO NOT USE IF
TAMPER-EVIDENT
OVERCAP IS NOT INTACT
300064651-1123
Store upright

INVELTYS®
(loteprednol etabonate
ophthalmic suspension) 1%
Sterile
NDC 71571-121-28 Rx Only
Alcon Laboratories, Inc.